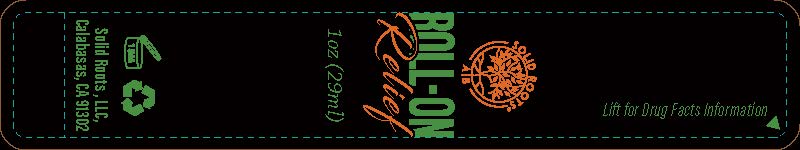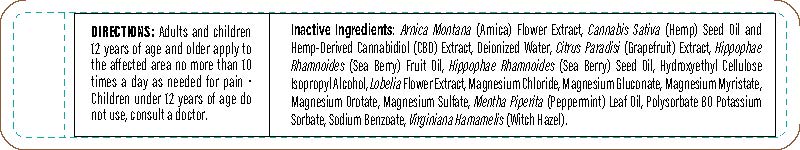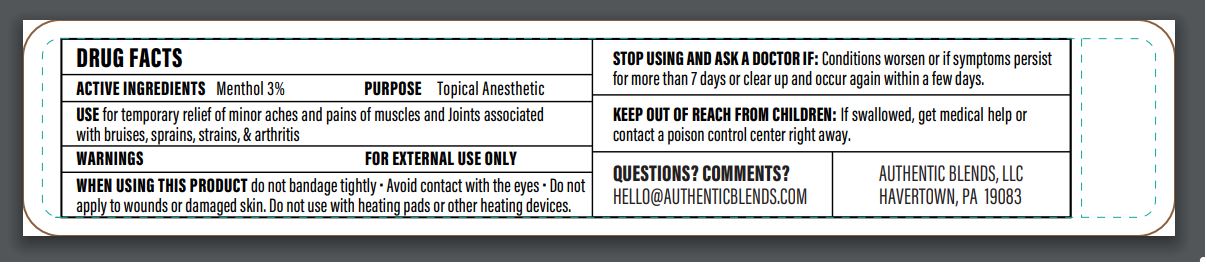 DRUG LABEL: SOLID ROOTS ROLL-ON RELIEF
NDC: 76348-481 | Form: LIQUID
Manufacturer: RENU LABORATORIES, INC.
Category: otc | Type: HUMAN OTC DRUG LABEL
Date: 20220613

ACTIVE INGREDIENTS: MENTHOL 0.84 g/28 g
INACTIVE INGREDIENTS: GRAPEFRUIT; WATER; METHYLCELLULOSE (4000 CPS); PEPPERMINT OIL; CANNABIS SATIVA SEED OIL; MAGNESIUM OROTATE; LOBELIA INFLATA LEAF; MAGNESIUM GLUCONATE; MAGNESIUM CHLORIDE; ARNICA MONTANA; SODIUM BENZOATE; POTASSIUM SORBATE; POLYSORBATE 80; HIPPOPHAE RHAMNOIDES SEED OIL; ISOPROPYL ALCOHOL; CANNABIDIOL; MAGNESIUM SULFATE, UNSPECIFIED; HIPPOPHAE RHAMNOIDES FRUIT OIL; WITCH HAZEL; MAGNESIUM MYRISTATE

Solid Roots AUTHENTIC BLENDS Roll-On Relief

ACTIVE INGREDIENT

Menthol 3 percent

PURPOSE

Topical Anesthetic

Uses

for temporary relief of minor aches and pains of muscles and joints associated with

- bruises
- sprains
- arthritis
- strains

RECENT MAJOR CHANGES

Change that is not substantive (Date change for a cloned submission

Dosage and Administration - only a date change

WARNINGS

For external use only

WHEN USING

Do not bandage tightly

Avoid contact with eyes

Do not apply to wounds or damaged skin

Do not use with heating pads or other heating devices

Stop use and ask a doctor if

Condition worsens or if symptoms persist for more than 7 days or clear up and occur again within a few days

KEEP OUT OF REACH OF CHILDREN

If swallowed, get medical help or contact a Poison Control Center right away.

DOSAGE AND ADMINISTRATION

Adults and children twelve years of age and older,

apply to affected area no more than ten times a day as needed for pain

children under twelve years of age do not use, consult a doctor

INACTIVE INGREDIENT

Arnica Montana (Arnica) Flower Extract, Cannabis Sativa (Hemp) Seed Oil and Hemp Derived Cannabidiol (CBD) Extract, Deionized Water, Citrus Paradisi (Grapefruit) Extract, Hippophae Rhamnoides (Sea Berry) Fruit Oil, Hippophae Rhamnoides (Sea Berry) Seed Oil, Hydroxyethyl Cellulose, Isopropyl Alcohol, Lobelia Flower Extract, Magnesium Chloride, Magnesium Gluconate, Magnesium Myristate, Magnesium Orotate, Magnesium Sulfate, Menth Piperita (Peppermint) Leaf Oil, Polysorbate 80, Potassium Sorbate, Sodium Benzoate, Hamamelis Virginiana (Witch Hazel)

Questions? Comments ?

HELLO@AUTHENTICBLENDS.COM

AUTHENTIC BLENDS, LLC

HAVERTOWN, PA 19083

PRODUCT MULTI-LAYER LABEL Page 1 of 3 Page 2 of 3 Page 3 of 3

LABEL IS A MULTI-LAYER. PAGE 1, PAGE 2 AND PAGE 3 ALL PART OF THE PEEL BACK LABEL